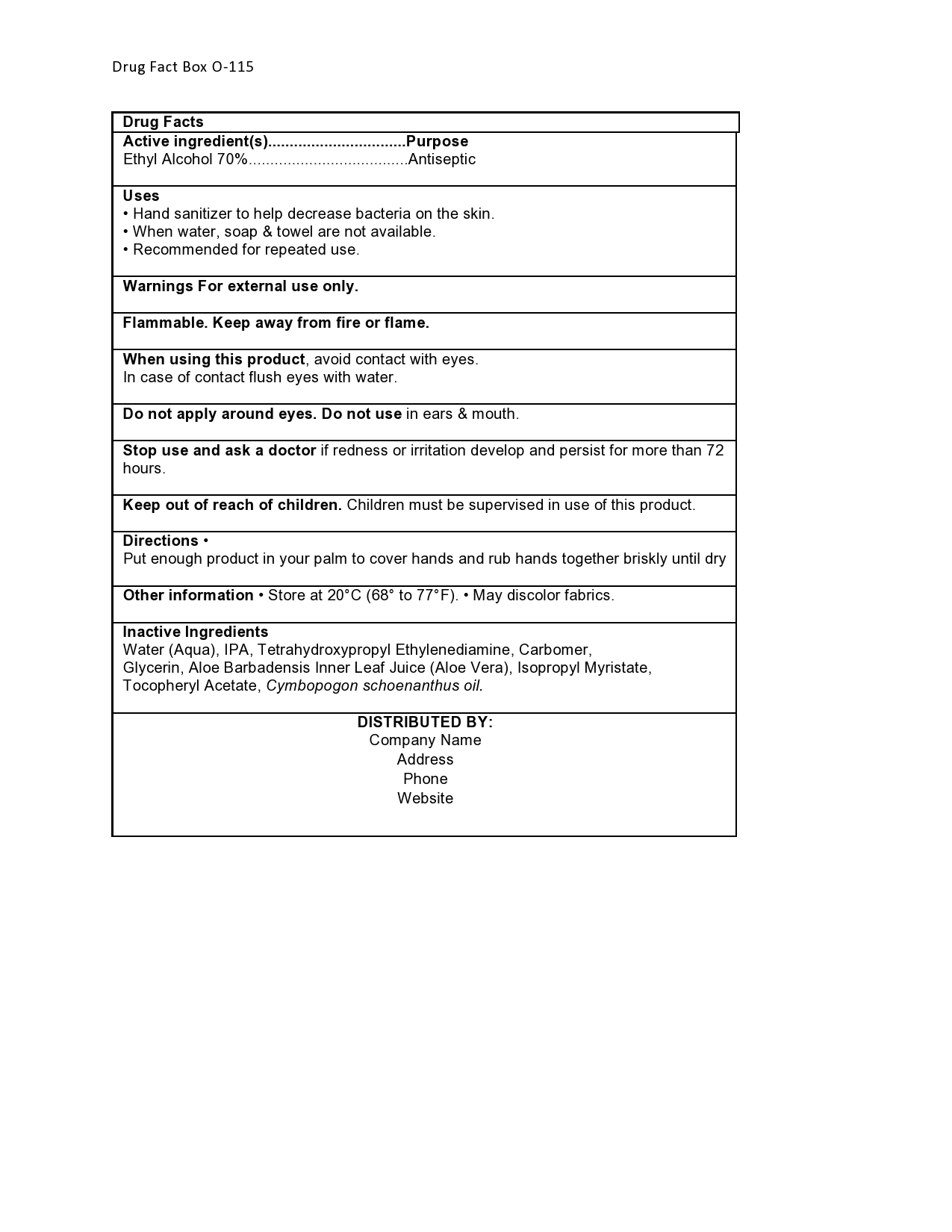 DRUG LABEL: Hand Sanitizer
NDC: 46432-121 | Form: GEL
Manufacturer: Dhaliwal Laboratories, LLC
Category: otc | Type: HUMAN OTC DRUG LABEL
Date: 20201226

ACTIVE INGREDIENTS: ALCOHOL 0.7 g/1 g
INACTIVE INGREDIENTS: WATER; ALOE VERA LEAF; ISOPROPYL ALCOHOL; CYMBOPOGON CITRATUS LEAF; GLYCERIN; CARBOMER 940; ALPHA-TOCOPHEROL ACETATE; ISOPROPYL MYRISTATE; EDETOL

Hand Sanitizer

Active Ingredients

Active ingredient | Purpose
Ethyl Alcohol 70% | Antiseptic

Inactive Ingredients

Water (Aqua)

Aloe Barbadensis Leaf Juice (Stabilized* Aloe Vera Gel)

Isopropyl Alcohol

Glycerin

Tetrahydroxypropyl Ethylenediamine

Acrylates/C10-30 Alkyl Acrylate Crosspolymer

Tocopheryl Acetate
Isopropyl Myristate.

Purpose Section

Uses

• Hand sanitizer to help decrease bacteria on the skin.

• When water, soap & towel are not available.

• Recommended for repeated use.

Warnings

For external use only.

Flammable. Keep away from fire or flame.

Indications & Usage

When using this product, avoid contact with eyes.

In case of contact flush eyes with water.

Do not apply around eyes. Do not use in ears & mouth.

Stop use and ask a doctor if

- Stop use and ask a doctor if redness or irritation develop and persist for more than 72 hours

Keep out of reach of children. Children must be supervised in use of this product.

Dosage & Administration Directions

Directions

- wet hands thoroughly with product
- briskly rub hands together until dry
- children under 6 years of age should be supervised when using this product

Other information

- store at 20 °C to 25 °C (68°F to 77°F) when possible. Do not store above 40 °C (104° F).
- may discolor certain fabrics